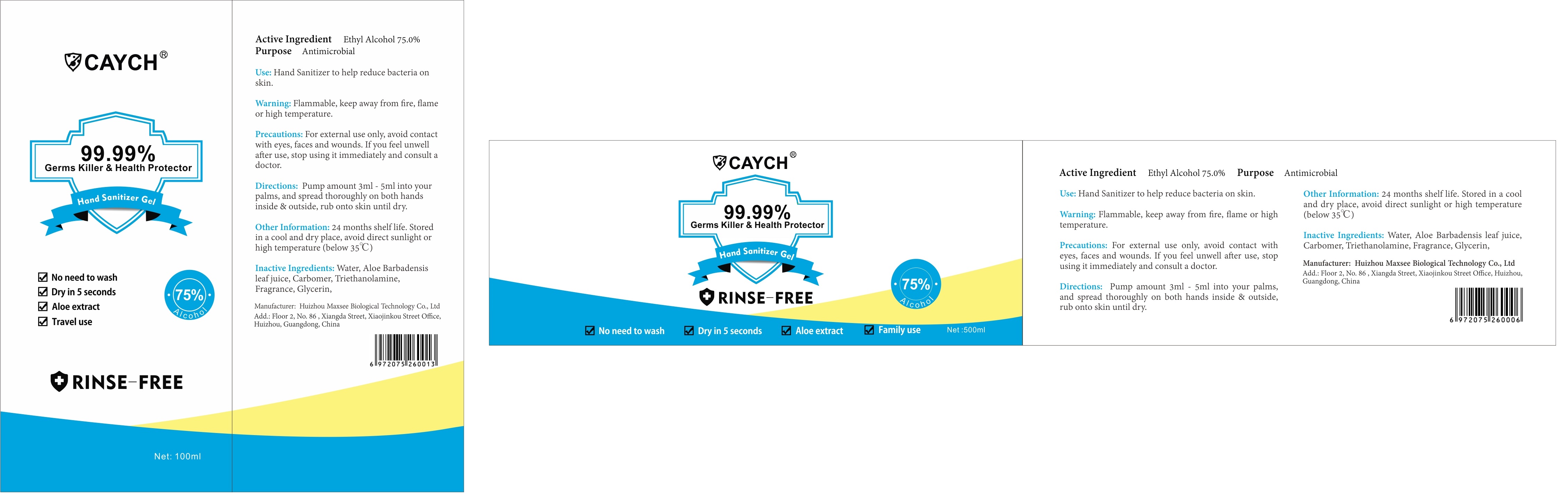 DRUG LABEL: Hand Sanitizer
NDC: 75389-005 | Form: GEL
Manufacturer: Huizhou Maxsee Biological Technology Co.,Ltd.
Category: otc | Type: HUMAN OTC DRUG LABEL
Date: 20200424

ACTIVE INGREDIENTS: ALCOHOL 75 mL/100 mL
INACTIVE INGREDIENTS: ALOE VERA LEAF 0.2 g/100 mL; GLYCERIN 0.5 g/100 mL; CARBOMER 934 0.4 g/100 mL; WATER; TROLAMINE 0.4 g/100 mL

Hand Sanitizer Gel

Active Ingredient

Ethyl Alcohol 75.0%

Purpose

Antimicrobial

Use

Hand Sanitizer to help reduce bacteria on skin

Warning

Flammable, keep away from fire, flame or high temperature

Precautions

For external use only, avoid contact with eves, faces and wounds. If you feel unwell after use, stop using it immediately and consult a doctor

Directions

Pump amount 3 ml- 5 ml into your palms, and spread thoroughly on both hands inside outside, rub onto skin until dry

Other information

24 months shelf life. Stored in a cool and dry place, avoid direct sunlight or high temperature(below 35 C)

Inactive ingredients

Water, Aloe Barbadensis leaf juice, Carbomer, Triethanolamine Fragrance, Glycerin,